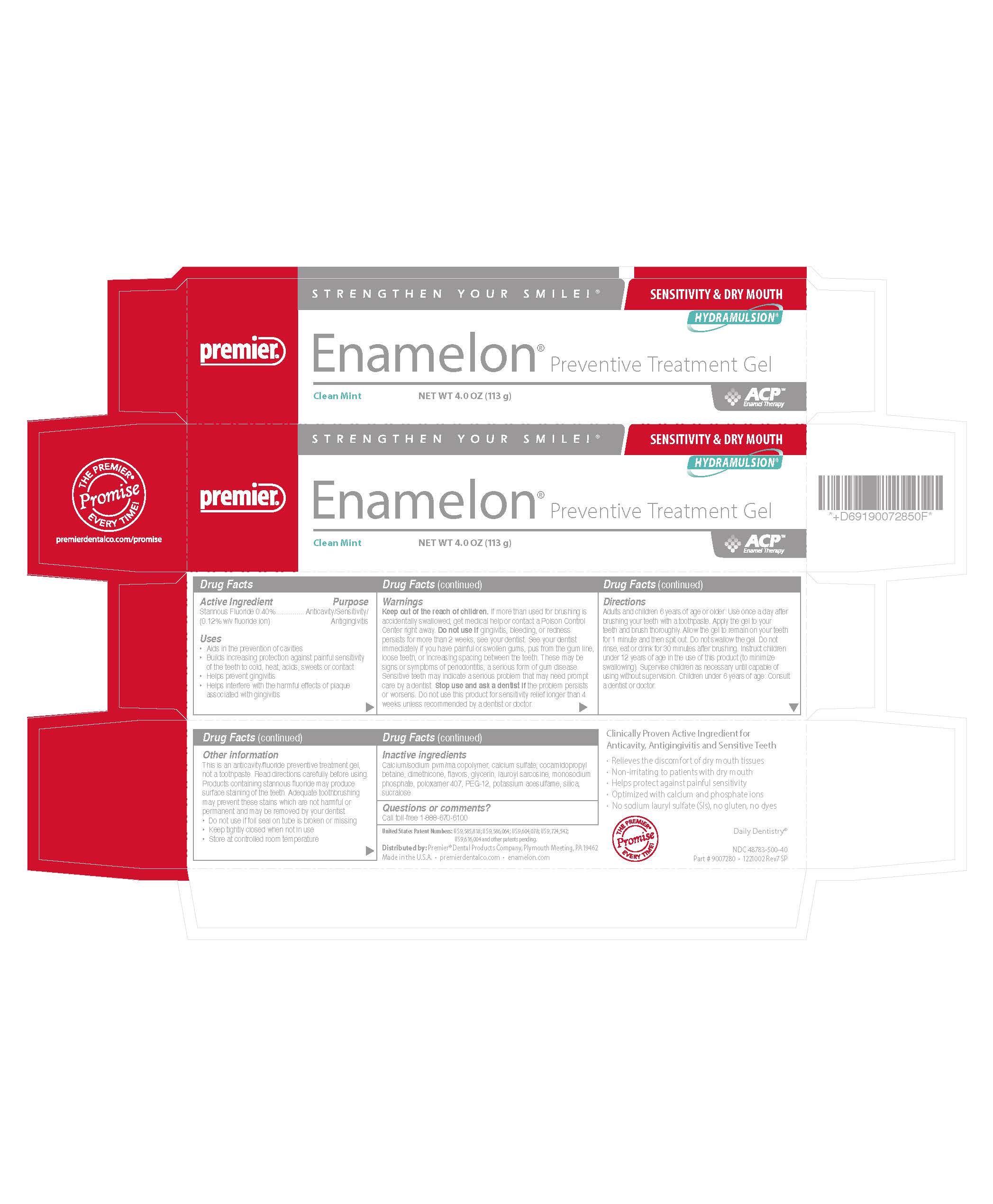 DRUG LABEL: Enamelon Preventive Treatment
NDC: 48783-500 | Form: GEL
Manufacturer: Premier Dental Products Company
Category: otc | Type: HUMAN OTC DRUG LABEL
Date: 20260113

ACTIVE INGREDIENTS: STANNOUS FLUORIDE 0.004 g/1 g
INACTIVE INGREDIENTS: ACESULFAME POTASSIUM; CALCIUM SULFATE; CALCIUM/SODIUM MALEATE METHYL VINYL ETHER COPOLYMER (1000000 MW, 1900 MPA.S AT 11%); COCAMIDOPROPYL BETAINE; DIMETHICONE; GLYCERIN; LAUROYL SARCOSINE; SODIUM PHOSPHATE, MONOBASIC; POLOXAMER 407; POLYETHYLENE GLYCOL, UNSPECIFIED; SILICON DIOXIDE; SUCRALOSE

Enamelon Gel

Active ingredient

Stannous fluoride 0.40% (0.15% w/v fluoride ion)

Purpose

Anticavity/Sensitivity Relief/Antigingivitis

Uses

- Aids in the prevention of cavities
- Builds increasing protection against painful sensitivity of the teeth to cold, heat, acids, sweets or contact
- Helps prevent gingivitis
- Helps interfere with the harmful effects of plaque associated with gingivitis

Warnings

Keep out of the reach of children.

WARNINGS

If more than used for brushing is accidentally swallowed, get medical help or contact a Poison Control Center right away. Do not use if gingivitis, bleeding, or redness persists for more than 2 weeks, see your dentist. See your dentist immediately if you have painful or swollen gums, pus from the gum line, loose teeth, or increasing spacing between the teeth. These may be signs or symptoms of periodontitis, a serious form of gum disease. Sensitive teeth may indicate a serious problem that may need prompt care by a dentist. Stop use and ask a dentist if the problem persists or worsens. Do not use this product for sensitivity relief longer than 4 weeks unless recommended by a dentist or doctor.

Directions

Adults and children 6 years of age or older: Use once a day after brushing your teeth with a toothpaste. Apply the gel to your teeth and brush thoroughly. Allow the gel to remain on your teeth for 1 minute and then spit out. Do not swallow the gel. Do not rinse, eat or drink for 30 minutes after brushing. Instruct children under 12 years of age in the use of this product (to minimize swallowing). Supervise children as necessary until capable of using without supervision. Children under 6 years of age: Consult a dentist or doctor.

Other information

This is an anticavity/fluoride preventive treatment gel, not a toothpaste. Read directions carefully before using. Products containing stannous fluoride may produce surface staining of the teeth. Adequate toothbrushing may prevent these stains which are not harmful or permanent and may be removed by your dentist.

- Do not use if foil seal is broken or missing
- Keep tightly closed when not in use
- Store at controlled room temperature

Inactive ingredients

Acesulfame K, calcium/sodium maleate methyl vinyl ether copolymer, calcium sulfate, cocamidopropyl betaine, dimethicone, flavors, glycerin, lauroyl-sarcosine, monosodium phosphate, poloxamer 407, polyethylene glycol, silica, sucralose

Questions or comments?

Call toll-free 1-888-670-6100
Monday-Thursday 8am-5pm EST, Friday 8am-4pm EST

United States Patent Numbers: US 5,993,784, US 5,711,936, US 5,651,959 and other patents pending. Made in U.S.A.

Ultramulsion® is a registered trademark of WhiteHill Oral Technologies, Inc.

Clinically Proven Active Ingredient for Anticavity, Antigingivitis and Sensitive Teeth

- Relieves the discomfort of dry mouth tissues
- Non-irritating to patients with dry mouth
- Optimized with calcium and phosphate ions
- No Sodium Lauryl Sulfate (SLS), No Gluten, No Dyes

Distributed by:

Premier® Dental Products Company, Plymouth Meeting, PA 19462

www.premusa.com Part # 9007285 www.enamelon.com

NDC 48783-500-40 021665 Rev4 SP

PRINCIPAL DISPLAY PANEL

STRENGTHEN YOUR SMILE!

ACPTM Enamel Therapy

Premier®

Enamelon®

Preventive Treatment Gel

NET WT 4.0 OZ (113 g)

SENSITIVITY & DRY MOUTH

Clean Mint

HYDRAMULSION®